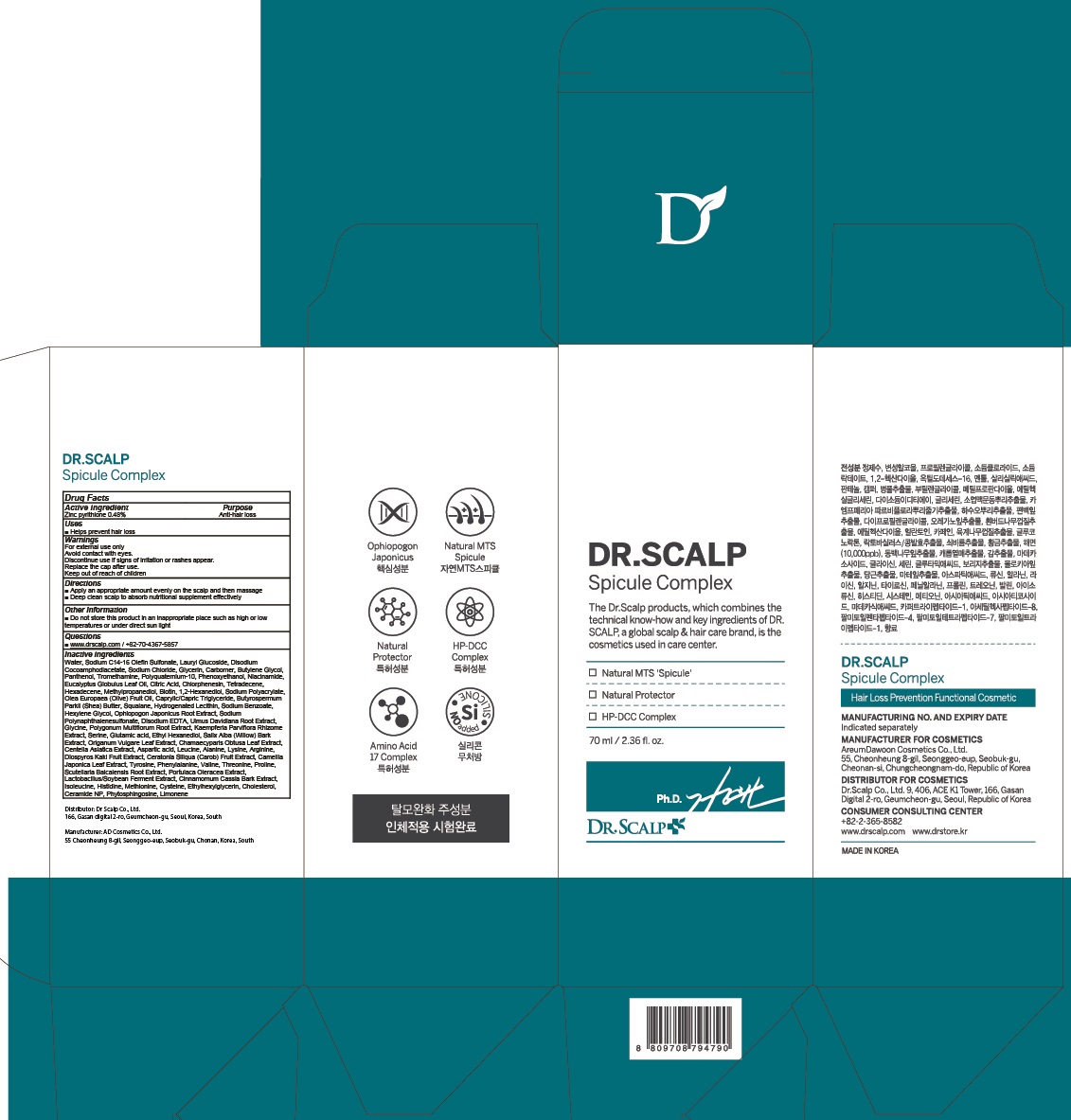 DRUG LABEL: DR. SCALP SPICULE COMPLEX
NDC: 82343-020 | Form: LIQUID
Manufacturer: Dr Scalp Co., Ltd.
Category: otc | Type: HUMAN OTC DRUG LABEL
Date: 20211103

ACTIVE INGREDIENTS: Salicylic acid 0.17 g/70 mL
INACTIVE INGREDIENTS: Water; Propylene Glycol; Sodium Chloride

ACTIVE INGREDIENT

Salicylic acid 0.25%

PURPOSE

Anti-hair loss

Uses

■ Helps prevent hair loss

WARNINGS

For external use only
Avoid contact with eyes.
Discontinue use if signs of irritation or rashes appear.
Replace the cap after use.
Keep out of reach of children

KEEP OUT OF REACH OF CHILDREN

Directions

■ Apply on scalp where hair loss treatment is urgently needed.
■ For best results use at least once a day

Other Information

■ Do not store this product in an inappropriate place such as high or low temperatures or under direct sun light

Questions

■ www.drscalp.com / +82-70-4367-5857

INACTIVE INGREDIENTS

Water, Alcohol Denat., Propylene Glycol, Sodium Chloride, Sodium Lactate, Butylene Glycol, 1,2-Hexanediol, Octyldodeceth-16, Menthol, Camphor, Centella Asiatica Extract, Fragrance, Panthenol, Methylpropanediol, Gluconolactone, Caffeine, Allantoin, Ethylhexylglycerin, Ophiopogon Japonicus Root Extract, Glycerin, Disodium EDTA, Glycine, Polygonum Multiflorum Root Extract, Kaempferia Parviflora Rhizome Extract, Serine, Glutamic acid, Ethyl Hexanediol, Ilex Paraguariensis Leaf Extract, Daucus Carota Sativa (Carrot) Root Extract, Corchorus Olitorius Leaf Extract, Borago Officinalis Extract, Dipropylene Glycol, Aspartic acid, Leucine, Alanine, Lysine, Arginine, Diospyros Kaki Fruit Extract, Ceratonia Siliqua (Carob) Fruit Extract, Camellia Japonica Leaf Extract, Tyrosine, Phenylalanine, Valine, Threonine, Proline, Madecassoside, Isoleucine, Salix Alba (Willow) Bark Extract, Origanum Vulgare Leaf Extract, Chamaecyparis Obtusa Leaf Extract, Sponge, Histidine, Methionine, Cysteine, Scutellaria Baicalensis Root Extract, Portulaca Oleracea Extract, Lactobacillus/Soybean Ferment Extract, Cinnamomum Cassia Bark Extract, Madecassic Acid, Asiaticoside, Asiatic Acid, Copper Tripeptide-1, Palmitoyl Pentapeptide-4, Acetyl Hexapeptide-8, Palmitoyl Tripeptide-1, Palmitoyl Tetrapeptide-7